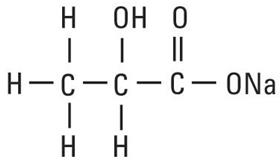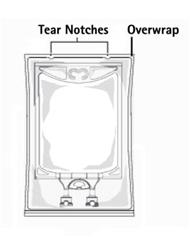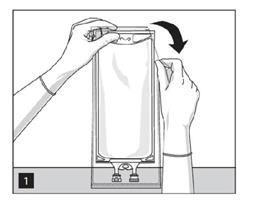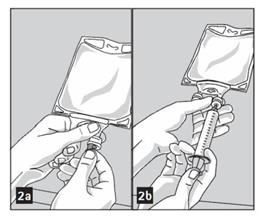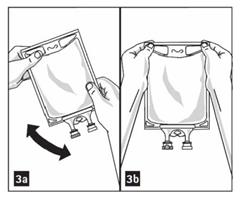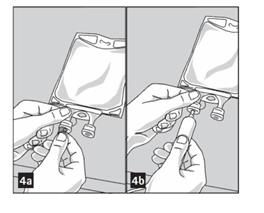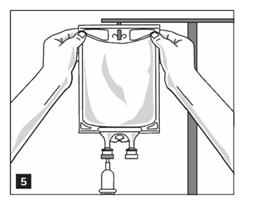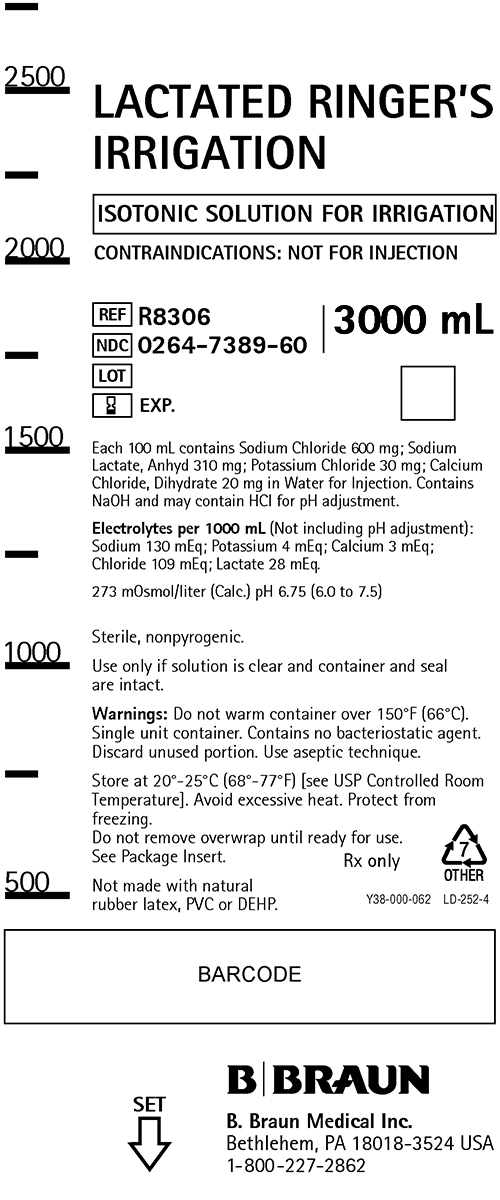 DRUG LABEL: Lactated Ringers Irrigation
NDC: 0264-7389 | Form: SOLUTION
Manufacturer: B. Braun Medical Inc.
Category: prescription | Type: HUMAN PRESCRIPTION DRUG LABEL
Date: 20210806

ACTIVE INGREDIENTS: SODIUM CHLORIDE 600 mg/100 mL; SODIUM LACTATE 310 mg/100 mL; POTASSIUM CHLORIDE 30 mg/100 mL; CALCIUM CHLORIDE 20 mg/100 mL
INACTIVE INGREDIENTS: WATER

Lactated Ringer's Irrigation
FOR ALL GENERAL IRRIGATION, WASHING AND RINSING PURPOSES
Not For Injection By Usual Parenteral Routes
Flexible Irrigation Container

DESCRIPTION

Lactated Ringer’s Irrigation is a sterile, nonpyrogenic solution of electrolytes in water for injection intended only for sterile irrigation, washing and rinsing purposes. The composition is based on a modification of the injectable formula originally known as Hartmann’s Solution.

Each 100 mL of Lactated Ringer’s Irrigation contains: Sodium chloride 600 mg; sodium lactate, anhydrous 310 mg; potassium chloride 30 mg; calcium chloride, dihydrate 20 mg. The pH is 6.75 (6.0 — 7.5). The solution is isotonic (273 mOsmol/liter, calc.) and has the following electrolyte content (mEq/liter): Sodium (Na^+) 130; potassium (K^+) 4; calcium (Ca^++) 3; chloride (Cl¯) 109 and lactate (CH3CH(OH)COO¯) 28. Contains sodium hydroxide and may contain hydrochloric acid for pH adjustment.

The solution contains no bacteriostatic or antimicrobial agent or added buffer and is intended only for use as a single-dose or short procedure irrigation. When smaller volumes are required, the unused portion should be discarded. Lactated Ringer’s Irrigation may be classified as a sterile irrigant, wash, rinse and pharmaceutical vehicle.

Calcium Chloride, USP is chemically designated calcium chloride, dihydrate (CaCl2 • 2H2O), white fragments or granules freely soluble in water.

Potassium Chloride, USP is chemically designated KCl, a white granular powder freely soluble in water.

Sodium Chloride, USP is chemically designated NaCl, a white crystalline powder freely soluble in water.

Sodium Lactate, USP is chemically designated C3H5NaO3, a 60% aqueous solution miscible in water.

It has the following structural formula:

Water for Injection, USP is chemically designated H2O.

The plastic container is made from a multilayered film specifically developed for parenteral drugs. It contains no plasticizers. The solution contact layer is a rubberized copolymer of ethylene and propylene. The container-solution unit is a closed system and is not dependent upon entry of external air during administration. The container is overwrapped to provide protection from the physical environment and to provide an additional moisture barrier when necessary.

Not made with natural rubber latex, PVC or DEHP.

CLINICAL PHARMACOLOGY

Lactated Ringer’s Irrigation exerts a mechanical cleansing action for sterile irrigation of body cavities, tissues or wounds, indwelling urethral catheters and surgical drainage tubes, and for washing, rinsing or soaking surgical dressings, instruments and laboratory specimens. It also serves as a vehicle for drugs used for irrigation or other pharmaceutical preparations.

Lactated Ringer’s Irrigation provides an isotonic irrigation with the same ionic constituents as Lactated Ringer’s Injection, USP, a modification of Hartmann’s Solution.

Lactated Ringer’s Irrigation is considered generally compatible with living tissues and organs.

Calcium chloride in water dissociates to provide calcium (Ca^++) and chloride (Cl¯) ions. They are normal constituents of the body fluids and are dependent on various physiologic mechanisms for maintenance of balance between intake and output. Approximately 80% of body calcium is excreted in the feces as insoluble salts; urinary excretion accounts for the remaining 20%.

Potassium chloride in water dissociates to provide potassium (K^+) and chloride (Cl¯) ions. Potassium is the chief cation of body cells (160 mEq/liter of intracellular water). It is found in low concentration in plasma and extracellular fluids (3.5 to 5.0 mEq/liter in a healthy adult). Potassium plays an important role in electrolyte balance.

Normally about 80 to 90% of the potassium intake is excreted in the urine; the remainder in the stools and to a small extent, in the perspiration. The kidney does not conserve potassium well so that during fasting or in patients on a potassium-free diet, potassium loss from the body continues resulting in potassium depletion.

Sodium chloride in water dissociates to provide sodium (Na^+) and chloride (Cl¯) ions. Sodium (Na^+) is the principal cation of the extracellular fluid and plays a large part in the therapy of fluid and electrolyte disturbances. Chloride (Cl¯) has an integral role in buffering action when oxygen and carbon dioxide exchange occurs in the red blood cells. The distribution and excretion of sodium (Na^+) and chloride (Cl¯) are largely under the control of the kidney which maintains a balance between intake and output.

Sodium lactate in water dissociates to provide sodium (Na^+) and lactate (C3H5O3¯) ions. The lactate anion provides an alkalizing effect resulting from simultaneous removal by the liver of lactate and hydrogen ions. In the liver, the lactate is metabolized to glycogen which is ultimately converted to carbon dioxide and water by oxidative metabolism.

The lactate anion acts as a source (alternate) of bicarbonate when normal production and utilization of lactic acid is not impaired as a result of disordered lactate metabolism. Since metabolic conversion is dependent on the integrity of cellular oxidative processes, lactate may be inadequate or ineffective as a source of bicarbonate in patients suffering from acidosis associated with shock or other disorders involving reduced perfusion of body tissues. When oxidative activity is intact, one to two hours time is required for metabolism of lactate.

Water is an essential constituent of all body tissues and accounts for approximately 70% of total body weight. Average normal adult daily requirement ranges from two to three liters (1 to 1.5 liters each for insensible water loss by perspiration and urine production).

Water balance is maintained by various regulatory mechanisms. Water distribution depends primarily on the concentration of electrolytes in the body compartments and sodium (Na^+) plays a major role in maintaining physiologic equilibrium.

INDICATIONS AND USAGE

Lactated Ringer’s Irrigation is indicated for all general irrigation, washing and rinsing purposes which permit use of a sterile, nonpyrogenic electrolyte solution.

CONTRAINDICATIONS

NOT FOR INJECTION BY USUAL PARENTERAL ROUTES.

An electrolyte solution should not be used for irrigation during electrosurgical procedures.

WARNINGS

FOR IRRIGATION ONLY. NOT FOR INJECTION.

Irrigating fluids have been demonstrated to enter the systemic circulation in relatively large volumes; thus this irrigation must be regarded as a systemic drug. Absorption of large amounts can cause fluid and/or solute overloading resulting in dilution of serum electrolyte concentrations, overhydration, congested states or pulmonary edema.

The risk of dilutional states is inversely proportional to the electrolyte concentrations of administered parenteral solutions. The risk of solute overload causing congested states with peripheral and pulmonary edema is directly proportional to the electrolyte concentrations of such solutions.

Do not warm container over 150°F (66°C).

PRECAUTIONS

Do not use for irrigation that may result in absorption into the blood.

Caution should be observed when the solution is used for continuous irrigation or allowed to “dwell” inside body cavities because of possible absorption into the blood stream and the production of circulatory overload.

Aseptic technique is essential with the use of sterile solutions for irrigation of body cavities, wounds and urethral catheters or for wetting dressings that come in contact with body tissues.

The flexible container is designed for use with nonvented irrigation sets. When used for irrigation via irrigation equipment, the administration set should be attached promptly. Unused portions should be discarded and a fresh container of appropriate size used for the start-up of each cycle or repeat procedure. For repeated irrigations of urethral catheters, a separate container should be used for each patient.

Do not administer unless solution is clear and container is undamaged. Discard unused portion.

Pregnancy

Animal reproduction studies have not been conducted with Lactated Ringer’s Irrigation. It is also not known whether it can cause fetal harm when administered to a pregnant woman or can affect reproduction capacity. It should be given to a pregnant woman only if clearly needed.

Pediatric Use

The safety and effectiveness of Lactated Ringer’s Irrigation have not been established. Its limited use in pediatric patients has been inadequate to fully define proper dosage and limitations for use.

ADVERSE REACTIONS

Possible adverse effects arising from the irrigation of body cavities, tissues, or indwelling catheters and tubes are usually avoidable when proper procedures are followed. Displaced catheters or drainage tubes can lead to irrigation or infiltration of unintended structures or cavities. Excessive volume or pressure during irrigation of closed cavities may cause undue distension or disruption of tissues. Accidental contamination from careless technique may transmit infection.

Should any adverse reaction occur, discontinue the irrigant, evaluate the patient, institute appropriate therapeutic countermeasures and save the remainder of the fluid for examination if deemed necessary.

OVERDOSAGE

In the event of overhydration or solute overload, re-evaluate the patient and institute appropriate corrective measures. (See WARNINGS, PRECAUTIONS and ADVERSE REACTIONS.)

DOSAGE AND ADMINISTRATION

The dose is dependent upon the capacity or surface area of the structure to be irrigated and the nature of the procedure. When used as a vehicle for other drugs, the manufacturer’s recommendations should be followed.

Drug Interactions

Additives may be incompatible. Consult with pharmacist, if available. When introducing additives, use aseptic technique, mix thoroughly and do not store.

Parenteral drug products should be inspected visually for particulate matter and discoloration prior to administration, whenever solution container permits. (See PRECAUTIONS.)

HOW SUPPLIED

Lactated Ringer's Irrigation is supplied sterile and nonpyrogenic in single-dose 3000 mL flexible irrigation container packaged 4 per case.

NDC | REF | Size
0264-7389-60 | R8306 | 3000 mL

Exposure of pharmaceutical products to heat should be minimized. Avoid excessive heat. Protect from freezing. Store at 20°–25°C (68°–77°F) [see USP Controlled Room Temperature]; however, brief exposure up to 40°C does not adversely affect the product.

Do not warm container over 150°F (66°C).

Instructions for Preparation and Administration

Not for injection.

Not for use with pressurized irrigation systems.

Aseptic technique is required.

- Inspect irrigation bag: overwrap and primary bag.
- Do not use if overwrap has been damaged.
- Do not use unless solution is clear and closure is intact.

1. To open: Tear overwrap starting from the tear notches. (Figure 1)

2. Prepare medication port by removal of aluminum foil. (Figure 2a)

- Puncture resealable medication port by using 19 – 22 gauge needle and inject additive(s). (Figure 2b)

- Medication port must be swabbed with disinfection agent before re-puncturing.
- Mix solution and medication thoroughly. (Figure 3a)
- Check admixture visually for particulate matter. (Figure 3b)

For Irrigation purposes while using an infusion set:
3. Remove aluminum foil from outlet/set port at the bottom of container (Figure 4a) and attach administration set (Figure 4b): use non-vented infusion set or close air vent on a vented set. Refer to directions for use accompanying the administration set.

4. Hang bag on IV Pole. (Figure 5)

LD-442-3 Y36-002-962

Package Insert

Rx only

Revised: August 2018

B. Braun Medical Inc.
Bethlehem, PA 18018-3524 USA
1-800-227-2862

PRINCIPAL DISPLAY PANEL - 3 Liter Container

LACTATED RINGER’S IRRIGATION

ISOTONIC SOLUTION FOR IRRIGATION
CONTRAINDICATIONS: NOT FOR INJECTION

REF R8306
NDC 0264-7389-60
LOT
EXP.

3000 mL

Each 100 mL contains Sodium Chloride 600 mg; Sodium
Lactate, Anhyd 310 mg; Potassium Chloride 30 mg; Calcium
Chloride, Dihydrate 20 mg in Water for Injection. Contains
NaOH and may contain HCI for pH adjustment.

Electrolytes per 1000 mL (Not including pH adjustment):
Sodium 130 mEq; Potassium 4 mEq; Calcium 3 mEq;
Chloride 109 mEq; Lactate 28 mEq.

273 mOsmol/liter (Calc.) pH 6.75 (6.0 to 7.5)

Sterile, nonpyrogenic.

Use only if solution is clear and container and seal are intact.

Warnings: Do not warm container over 150°F (66°C).
Single unit container. Contains no bacteriostatic agent.
Discard unused portion. Use aseptic technique.

Store at 20°-25°C (68°-77°F) [see USP Controlled Room
Temperature]. Avoid excessive heat. Protect from freezing.
Do not remove overwrap until ready for use.
See Package Insert.

Not made with natural rubber latex, PVC or DEHP.

Rx only

Y38-000-062 LD-252-4

B. Braun Medical Inc.
Bethlehem, PA 18018-3524 USA
1-800-227-2862

SET

Lactated Ringer's Irrigation 3L Container Label